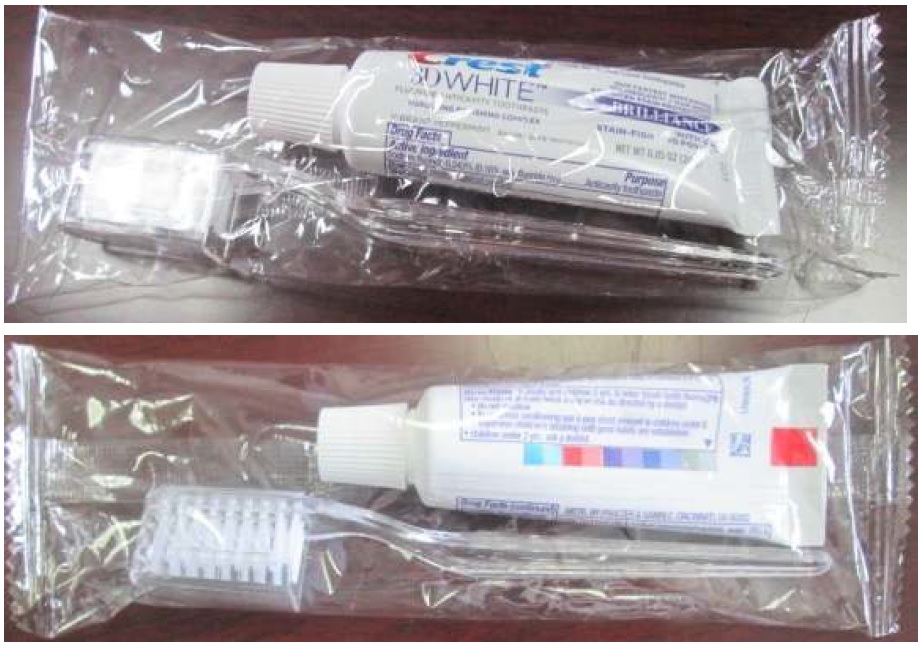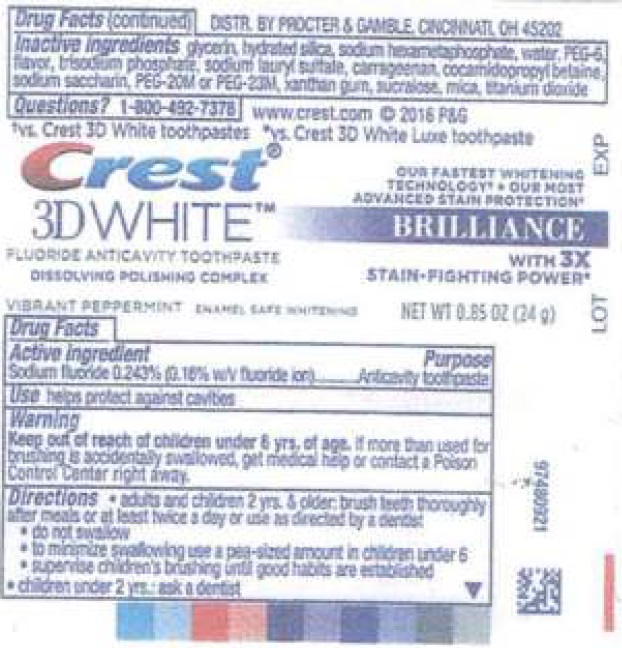 DRUG LABEL: Kit 2
NDC: 69491-080 | Form: KIT | Route: DENTAL
Manufacturer: Buzz Export Services Pty., Ltd.
Category: otc | Type: HUMAN OTC DRUG LABEL
Date: 20231221

ACTIVE INGREDIENTS: SODIUM FLUORIDE 2.43 mg/1 g
INACTIVE INGREDIENTS: HYDRATED SILICA; HEXASODIUM HEXAMETAPHOSPHATE; GLYCERIN; WATER; POLYETHYLENE GLYCOL 300; METHYL SALICYLATE; SODIUM LAURYL SULFATE; CARRAGEENAN; COCAMIDOPROPYL BETAINE; SACCHARIN SODIUM; POLYETHYLENE OXIDE 900000; XANTHAN GUM; SUCRALOSE; MICA; TITANIUM DIOXIDE

Kit 2

Active ingredient

Sodium fluoride 0.243% (0.16% w/v fluoride ion)

Purpose

Anticavity toothpaste

Use

helps protect against cavities

Warning

Keep out of reach of children

under 6 yrs. of age. if more than used for brushing is accidentally swallowed, get medical help or contact a Poison Control Center right away.

Directions

- adults and children 2 yrs. & older: brush teeth thoroughly after meals or at least tweice a day or use as directed by a dentist
- do not swallow
- to minimize swallowing use a pea-sized amount in children under 6
- children under 2 yrs: ask a dentist

Inactive ingredients

glycerin, hydrated silica, sodium hexametaphosphate, water, flavor, trisodium phosphate, sodium lauryl sulfate, carrageenan, cocamidopropyl betaine sodium saccharin, PEG-20M or PEG-23M, Xanthan gum, sucralose, mica, titanium dioxide

Questions?

1-800-492-7378